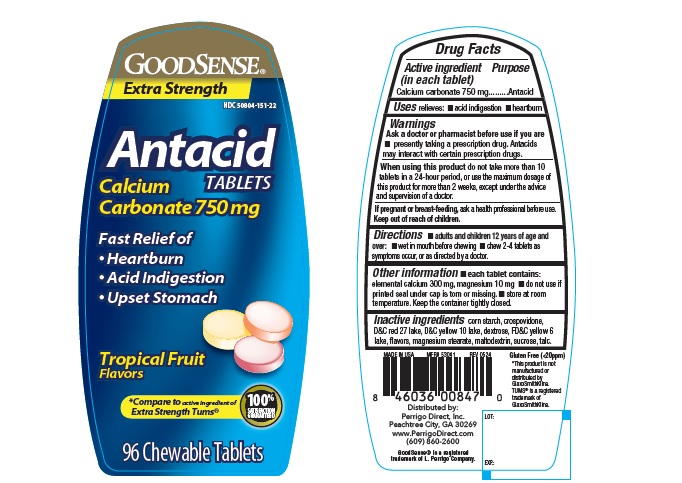 DRUG LABEL: Goodsense Extra Strength Antacid
NDC: 50804-151 | Form: TABLET, CHEWABLE
Manufacturer: GoodSense
Category: otc | Type: Human OTC Drug Label
Date: 20240913

ACTIVE INGREDIENTS: CALCIUM CARBONATE 750 mg/1 1
INACTIVE INGREDIENTS: STARCH, CORN; DEXTROSE, UNSPECIFIED FORM; MAGNESIUM STEARATE; MALTODEXTRIN; SUCROSE; TALC; CROSPOVIDONE; D&C RED NO. 27 ALUMINUM LAKE; D&C YELLOW NO. 10 ALUMINUM LAKE; FD&C YELLOW NO. 6 ALUMINUM LAKE

Good sense Extra Strength Antacid 127TF

ACTIVE INGREDIENT (in each tablet)

Calcium carbonate 750 mg

PURPOSE

Antacid

USE(S)

relieves:

- acid indigestion
- heartburn

WARNINGS

.

ASK A DOCTOR OR PHARMACIST BEFORE USE IF YOU ARE

- presently taking a prescription drug. Antacids may interact with certain prescription drugs.

WHEN USING THIS PRODUCT

do not take more than 10 tablets in a 24-hour period, or use the maximum dosage of this product for more than 2 weeks, except under the advice and supervision of a doctor.

IF PREGNANT OR/BREASTFEEDING,

ask a health professional before use.

KEEP OUT OF REACH OF CHILDREN

.

DIRECTIONS

- adults and children 12 years of age and over:
- wet in mouth before chewing
- chew 2-4 tablets as symptoms occur, or as directed by a doctor.

OTHER INFORMATION

- each tablet contains: elemental calcium 300 mg, magnesium 10mg
- do not use if printed seal under cap is torn or missing.
- store below 30°C (86°F).

INACTIVE INGREDIENTS

adipic acid, corn starch, crospovidone, dextrose, FD&C blue 1 lake, FD&C red 40 lake, flavors, magnesium stearate, maltodextrin, sucrose, talc.

PRINCIPAL DISPLAY PANEL

GOOD SENSE®

Extra Strength

NDC 50804-151-22

Antacid TABLETS

Calcium Carbonate 750mg

Fast Relief of

- Heartburn
- Acid Indigestion
- Upset Stomach

Tropical Fruit Flavors

*Compare to active ingredient of Extra Strength Tums®

96 Chewable Tablets